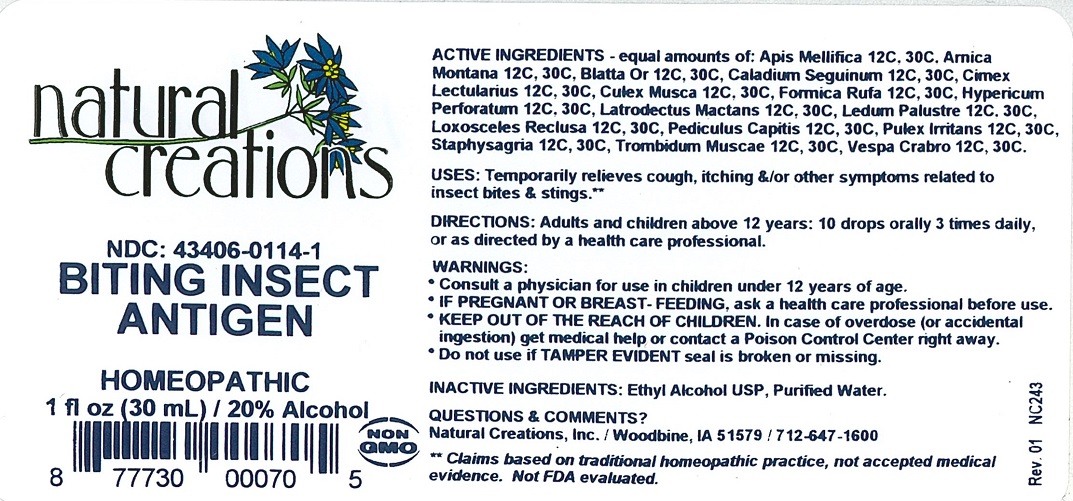 DRUG LABEL: BITING INSECT ANTIGEN
NDC: 43406-0114 | Form: LIQUID
Manufacturer: Natural Creations, Inc.
Category: homeopathic | Type: HUMAN OTC DRUG LABEL
Date: 20251113

ACTIVE INGREDIENTS: APIS MELLIFERA 12 [hp_C]/1 mL; ARNICA MONTANA 30 [hp_C]/1 mL; BLATTA ORIENTALIS 30 [hp_C]/1 mL; DIEFFENBACHIA SEGUINE 12 [hp_C]/1 mL; CIMEX LECTULARIUS 30 [hp_C]/1 mL; CULEX PIPIENS 30 [hp_C]/1 mL; FORMICA RUFA 30 [hp_C]/1 mL; HYPERICUM PERFORATUM 30 [hp_C]/1 mL; LATRODECTUS MACTANS 30 [hp_C]/1 mL; LEDUM PALUSTRE TWIG 30 [hp_C]/1 mL; LOXOSCELES RECLUSA 30 [hp_C]/1 mL; PEDICULUS HUMANUS VAR. CAPITIS 30 [hp_C]/1 mL; PULEX IRRITANS 30 [hp_C]/1 mL; DELPHINIUM STAPHISAGRIA SEED 30 [hp_C]/1 mL; VESPA CRABRO 30 [hp_C]/1 mL
INACTIVE INGREDIENTS: WATER; ALCOHOL

BITING INSECT ANTIGEN

ACTIVE INGREDIENT

ACTIVE INGREDIENTS - equal amounts of: Apis Mellifica 12C, 30C, Arnica Montana 12C, 30C, Blatta Or 12C, 30C, Caladium Seguinum 12C, Cimex Lectularius 12C, 30C, Culex Musca 12C, 30C, Formica Rufa 12C, 30C, Hypericum Perforatum 12C, 30C, Latrodectus Mactans 12C, 30C, Ledum Palustre 12C, 30C, Loxosceles Reclusa 12C, 30C, Pediculus Capitis 12C, 30C, Pulex Irritans 12C, 30C, Staphysagria 12C, 30C, Trombidum Muscae 12C, 30C, Vespa Crabro 12C, 30C.

PURPOSE

USES: Temporarily relieves cough, itching &/or other symptoms related to insect bites & stings.**

INDICATIONS AND USAGE

USES: Temporarily relieves cough, itching &/or other symptoms related to insect bites & stings.**

DOSAGE AND ADMINISTRATION

DIRECTIONS: Adults and children above 12 years: 10 drops orally 3 times daily, or as directed by a health care professional.

WARNINGS:

- Consult a physician for use in children under 12 years of age.
- IF PREGNANT OR BREAST-FEEDING,ask a health care professional before use.
- KEEP PUT OF THE REACH OF CHILDREN. In case of overdose (or accidental ingestion) get medical help or contact a Poison Control Center right away.
- Do not use if TAMPER EVIDENT seal is broken or missing.

KEEP OUT OF REACH OF CHILDREN

KEEP OUT OF THE REACH OF CHILDREN. In case of overdose (or accidental ingestion) get medical help or contact a Poison Control Center right away.

INACTIVE INGREDIENTS: Ethyl Alcohol USP, Purified Water.

QUESTIONS & COMMENTS?

Natural Creations, Inc. / Woodbine, IA 51579 / 712-647-1600

REFERENCES

**Claims based on traditional homeopathic practice, not accepted medical evidence. Not FDA evaluated.

PACKAGE LABEL

NDC: 43406-0114-1

BITING INSECT ANTIGEN

HOMEOPATHIC

1 fl oz (30 mL) / 20% Alcohol

UPC: 877730000705